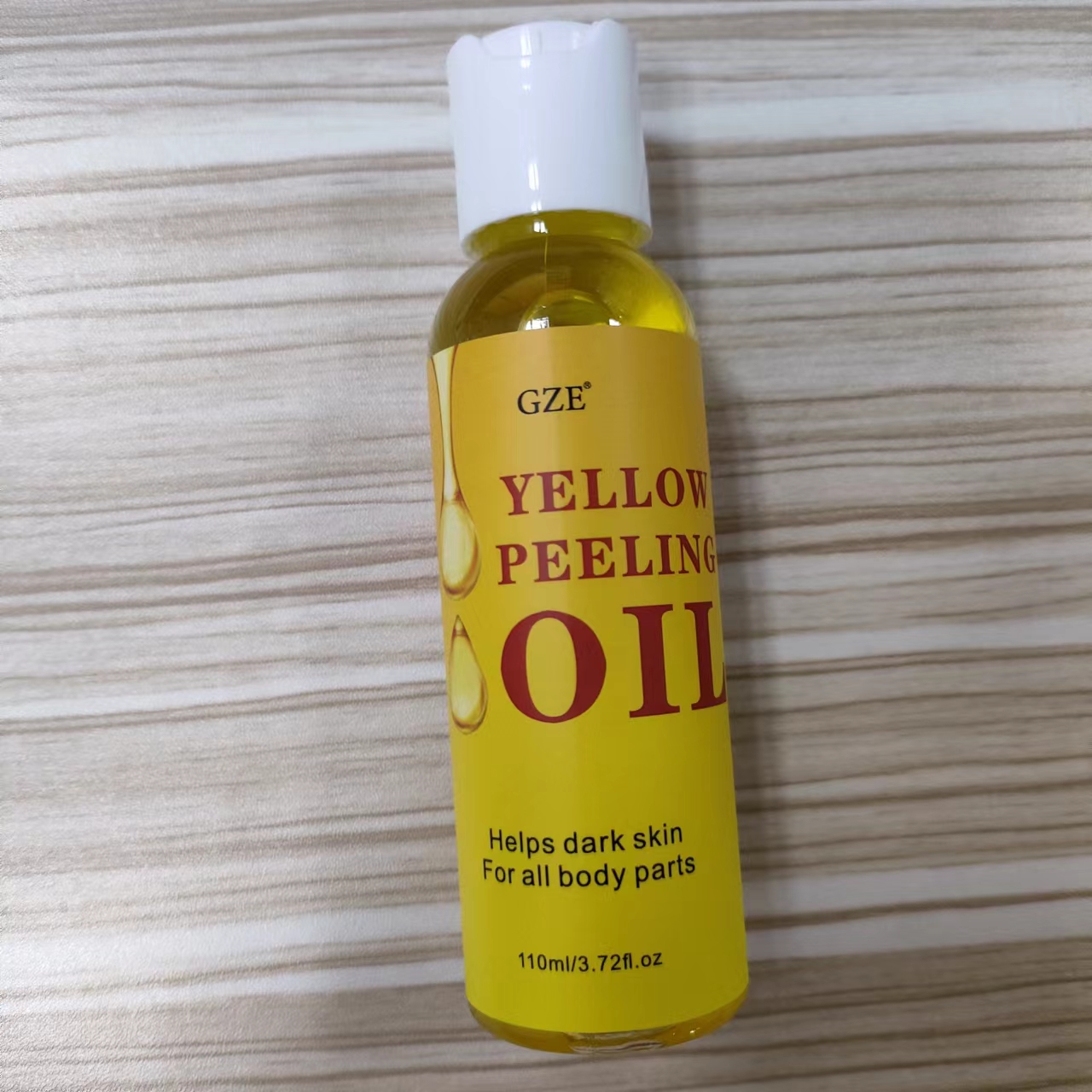 DRUG LABEL: GZE Yellow Peeling Oil
NDC: 74458-050 | Form: LIQUID
Manufacturer: Guangzhou Yilong Cosmetics Co., Ltd
Category: otc | Type: HUMAN OTC DRUG LABEL
Date: 20241110

ACTIVE INGREDIENTS: SERINE 2 g/100 mL; TAURINE 2 g/100 mL; SALICYLIC ACID 1.2 g/100 mL
INACTIVE INGREDIENTS: CENTELLA ASIATICA TRITERPENOIDS; CI 19140; HYDROXYACETOPHENONE; BUTYLENE GLYCOL; GLYCERIN; PROPYLENE GLYCOL; CHAMOMILE; PEG-400; 1,2-HEXANEDIOL; SODIUM HYALURONATE; BETAINE; POLYGONUM CUSPIDATUM ROOT EXTRACT; GREEN TEA LEAF; SCUTELLARIA BAICALENSIS ROOT; GLYCYRRHIZA GLABRA; PEG-40 HYDROGENATED CASTOR OIL; ROSMARINUS OFFICINALIS (ROSEMARY) LEAF EXTRACT

GZE YELLOW PEELIG OIL

ACTIVE INGREDIENT

Salicylic Acid 1.2%
Taurine 2%
Serine 2%

INACTIVE INGREDIENT

Propylene Glycol

PEG-400

Glycerin

Betaine

Sodium Hyaluronate

1,2 Hexanediol

Hydroxyacetophenone

Butylene Glycol

Centella Asiatica Extract

Polygonum Cuspidatum Root Extract

Scutellaria Baicalensis Root Extract

Camellia Sinensis Leaf Extract

Glycyrrhiza Glabra (Licorice) Root Extract

Chamomilla Recutita (Matricaria) Flower Extract

Rosmarinus Officinalis (Rosemary) Leaf Extract

PEG-40 Hydrogenated Castor Oil

Parfum

CI 19140

PURPOSE

Exfoliating.

INDICATIONS AND USAGE

Apply the yellow peeling oil evenly to the skin and wait for 15 minutes, rinse with water. Three times a day. lt is necessary to use the yellow oil skin peeling for 3-7 consecutive days.

WARNINGS

For external use only.

Stop use and ask a doctor if rash occurs.

Do not use on damaged or broken skin.

When using this product keep out of eyes. Rinse with water to remove.

DOSAGE AND ADMINISTRATION

Apply the yellow peeling oil evenly to the skin and wait for 15 minutes, rinse with water. Three times a day. lt is necessary to use the yellow oil skin peeling for 3-7 consecutive days.